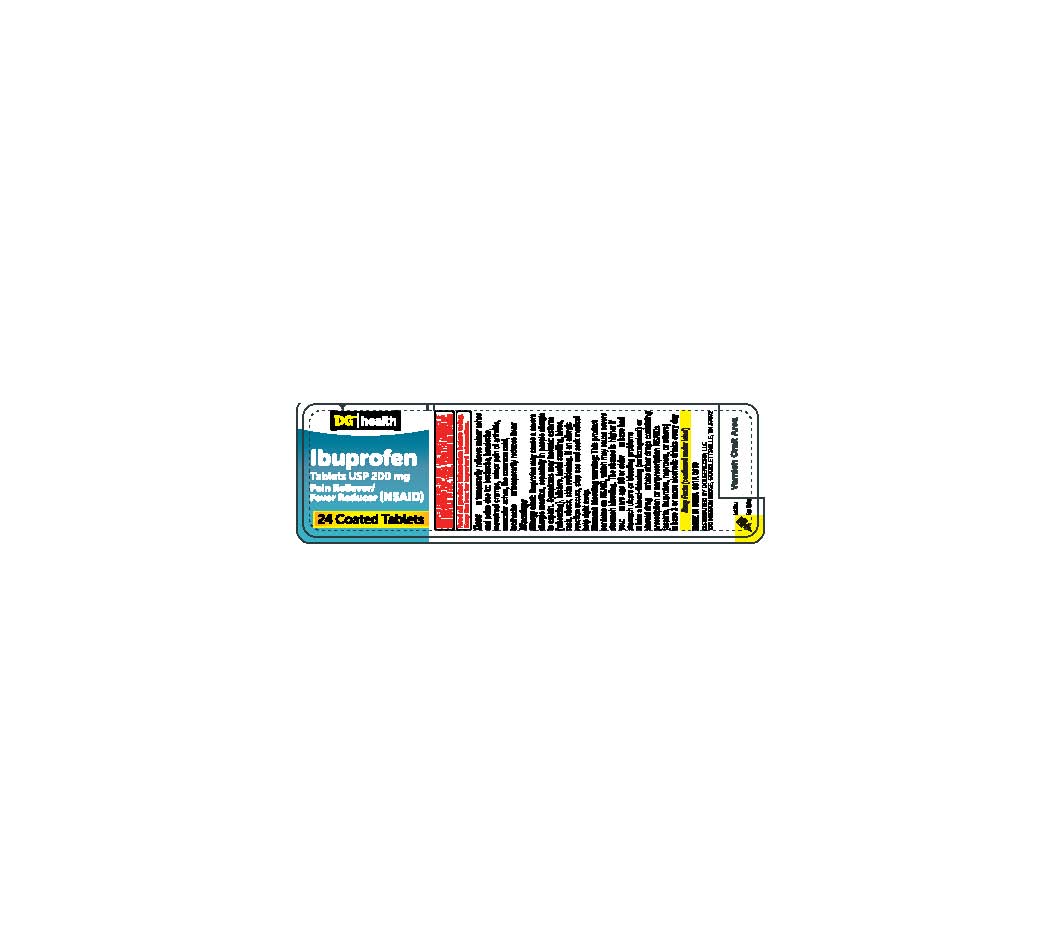 DRUG LABEL: ibuprofen
NDC: 55910-901 | Form: TABLET, COATED
Manufacturer: DOLGENCORP INC
Category: otc | Type: HUMAN OTC DRUG LABEL
Date: 20230102

ACTIVE INGREDIENTS: IBUPROFEN 200 mg/1 1
INACTIVE INGREDIENTS: CROSCARMELLOSE SODIUM; POLYETHYLENE GLYCOL, UNSPECIFIED; POLYVINYL ALCOHOL, UNSPECIFIED; SILICON DIOXIDE; FERRIC OXIDE RED; MAGNESIUM STEARATE; STARCH, CORN; TALC; TITANIUM DIOXIDE; MICROCRYSTALLINE CELLULOSE

601R-DOLLAR GENERAL - IBUPROFEN TABLETS 200 MG 55910-901

ACTIVE INGREDIENT

Ibuprofen 200 mg (NSAID)*

* nonstreoidal anti-inflammatory drug

INACTIVE INGREDIENT

Silicon dioxide, croscarmellose sodium, iron oxide red, magnesium stearate, microcrystalline cellulose, polyethylene glycol, polyvinyl alcohol, pregelatinized starch, talc, titanium dioxide.

PURPOSE

Pain reliever / fever reducer

INDICATIONS AND USAGE

USE(S)

temporarily relieves minor aches and pains due to :
backache
headache
menstrual cramps
minor pain of arthritis
muscular aches
the common cold
toothache
temporarily reduces fever

WARNINGS

Allergy alert: Ibuprofen may cause a severe allergic reaction, especially in people allergic to aspirin.
Symptoms may include:

asthma (wheezing)
blisters
facial swelling
hives
rash
shock
skin reddening

If an allergic reaction occurs, stop use and seek medical help right away.
Stomach bleeding warning: This product contains an NSAID, which may cause severe stomach bleeding. The chance is higher if you:

are age 60 or older
have had stomach ulcers or bleeding problems
take a blood-thinning (anticoagulant) or steroid drug
take other drugs containing prescription NSAIDs (aspirin, ibuprofen, naproxen, or others)
have 3 or more alcoholic drinks every day while using this product
take more or for a longer time than directed

Heart attack and stroke warning: NSAID's except aspirin increases the risk of heart attack, heart failure, and stroke. These can be fatal. The risk is higher if you use more than directed or longer than directed.

DIRECTIONS

do not take more than directed
the smallest effective dose should be used

adults and children 12 years and older:

take 1 tablet every 4 to 6 hours while symptoms persist
if pain or fever does not respond to 1 tablet, 2 tablets may be used
do not exceed 6 tablets in 24 hours, unless directed by a doctor.

Children under 12 years:

ask a doctor

KEEP OUT OF REACH OF CHILDREN

In case of overdose, get medical help or contact a Poison Control Center right away. (1-800-222-1222)